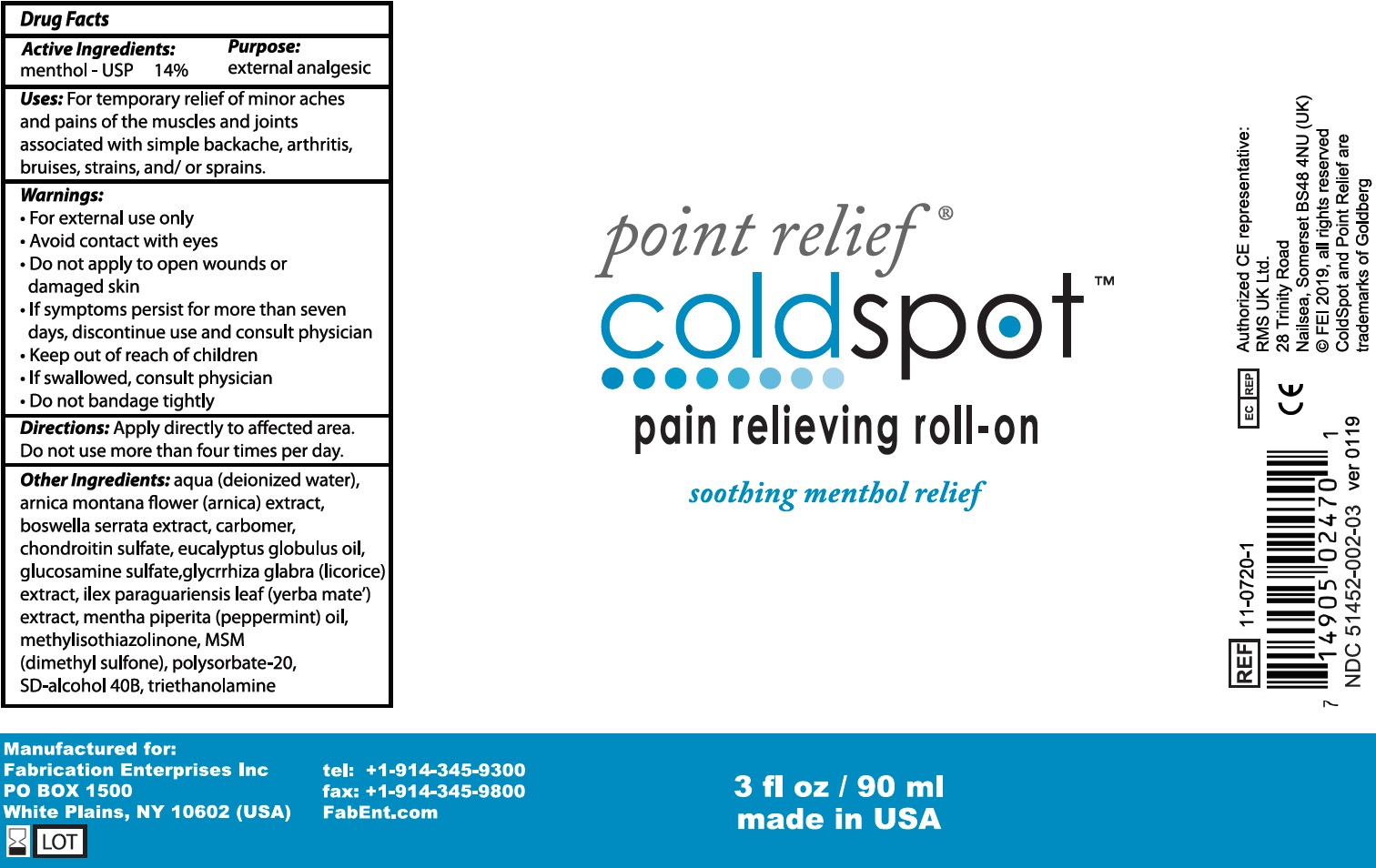 DRUG LABEL: Point Relief cold Spot Pain Relieving roll-on
NDC: 51452-037 | Form: LIQUID
Manufacturer: Fabrication Enterprises
Category: otc | Type: HUMAN OTC DRUG LABEL
Date: 20231105

ACTIVE INGREDIENTS: MENTHOL 140 mg/1 mL
INACTIVE INGREDIENTS: WATER; ARNICA MONTANA FLOWER; INDIAN FRANKINCENSE; CARBOXYPOLYMETHYLENE; EUCALYPTUS OIL; GLUCOSAMINE SULFATE; GLYCYRRHIZA GLABRA; ILEX PARAGUARIENSIS LEAF; PEPPERMINT OIL; METHYLISOTHIAZOLINONE; DIMETHYL SULFONE; POLYSORBATE 20; TROLAMINE

Point Relief cold Spot Pain Relieving roll-on

Active Ingredients:

menthol - USP 14%

Purpose:

external analgesic

Uses:

For temporary relief of minor aches and pains of the muscles and joints associated with simple backache, arthritis, bruises, strains, and/ or sprains.

Warnings:

- For external use only
- Avoid contact with eyes

Do not apply

- to open wounds or damaged skin
- If symptoms persist for more than sevan days, discontinue use and consult physician

Keep out of reach of children

- If swallowed, consult physician
- Do not bandage tightly

Directions:

Apply directly to affected area. Do not use more than four fimes per day.

Other Ingredients:

aqua (deionized water), arnica montana flower (arnica) extract, boswellia serrata extract, carbomer, chondroitin sulfate, eucalyptus globulus oil, glucosamine sulfate, glycrrhiza glabra (licorice) extract, ilex paraguariensis leaf (yerba mate) extract, mentha piperita (peppermint) oil, methylisothiazolinone, MSM (dimethyl sulfone), polysorbate-20, SD-alcohol 40B, triethanolamine